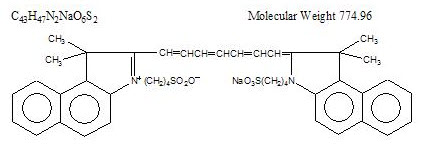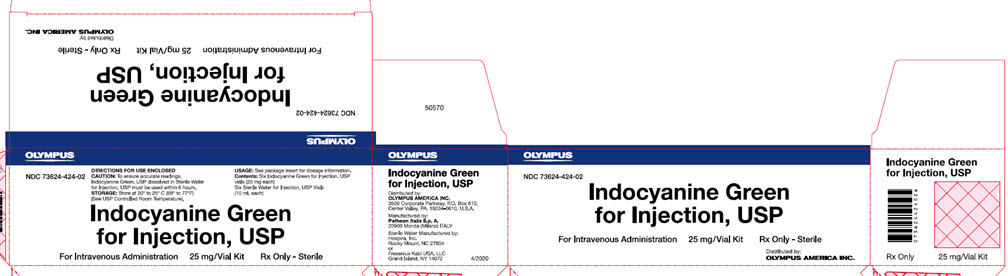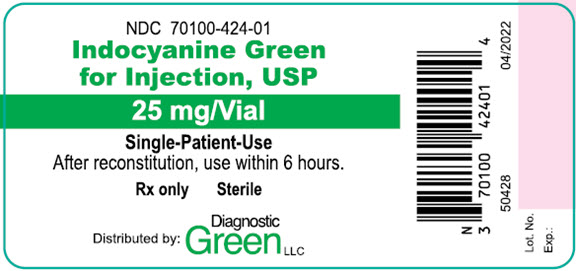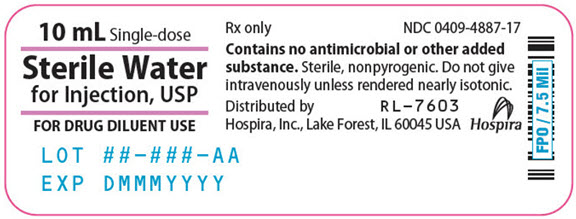 DRUG LABEL: Indocyanine Green
NDC: 73624-424 | Form: KIT | Route: INTRAVENOUS
Manufacturer: Olympus America, Inc.
Category: prescription | Type: HUMAN PRESCRIPTION DRUG LABEL
Date: 20200601

ACTIVE INGREDIENTS: INDOCYANINE GREEN 25 mg/1 1; WATER 1 mL/1 mL
INACTIVE INGREDIENTS: SODIUM IODIDE

HIGHLIGHTS OF PRESCRIBING INFORMATION

These highlights do not include all the information needed to use Indocyanine Green for Injection USP safely and effectively. See full prescribing information for Indocyanine Green for Injection USP.
Indocyanine Green for Injection USP Fore Intravenous Injection
Initial U.S. Approval: 1959

1 INDICATIONS AND USAGE

Indocyanine Green for Injection USP a tricarbocyanine dye, is indicated:

- For visual assessment of blood vessels, blood flow and related tissue perfusion with OLYMPUS infrared compatible endoscopic imaging system (1.1)
- For visual assessment of the major extrahepatic bile ducts with OLYMPUS infrared imaging endoscopic imaging system (1.2)
- For viewing intra-operative blood flow in the cerebral area with OLYMPUS infrared compatible video microscopic imaging system (1.3)

2 DOSAGE AND ADMINISTRATION

For visual assessment of blood vessels, blood flow and related tissue perfusion (2.1)

Under sterile conditions, the Indocyanine Green for Injection USP powder should be dissolved with the 10 mL Sterile Water for Injection, USP provided and the solution used within 6 hours after it is prepared. The usual doses of Indocyanine Green for Injection USP is 0.1 mg/kg (0.04 mL/kg) – 0.3 mg/kg (0.12 mL/kg). Immediately follow each ICG intravenous injection with a tight bolus injection of approximately 10 - 12 mL of normal saline immediately before IR imaging. Multiple administrations can be performed, up to 2 mg/kg (0.8 mL/kg) per patient.

For visual assessment of the major extrahepatic bile ducts (2.2)

Under sterile conditions, the Indocyanine Green for Injection USP powder should be dissolved with the 10 mL Sterile Water for Injection, USP provided and the solution used within 6 hours after it is prepared. The usual doses of Indocyanine Green for Injection USP is 3.0 mg (1.2 mL). Immediately follow each ICG intravenous injection with a tight bolus injection of approximately 10 - 12 mL of normal saline at least 30 minutes prior to IR imaging. Multiple administrations can be performed, up to 2 mg/kg (0.8 mL/kg) per patient.

For viewing intra-operative blood flow in the cerebral area (2.3)

Under sterile conditions, the Indocyanine Green for Injection USP powder should be dissolved with the 10 mL Sterile Water for Injection, USP provided and the solution used within 6 hours after it is prepared. The usual doses of Indocyanine Green for Injection USP is 0.1 mg/kg (0.04 mL/kg) – 0.3 mg/kg (0.12 mL/kg). Immediately follow each ICG intravenous injection with a tight bolus injection of approximately 10 - 12 mL of normal saline immediately before IR imaging Multiple administrations can be performed, up to 2 mg/kg (0.8 mL/kg) per patient.

3 DOSAGE FORMS AND STRENGTHS

Indocyanine Green for Injection USP is a sterile, lyophilized green powder containing 25 mg of indocyanine green with no more than 5% sodium iodide. (3)

4 CONTRAINDICATIONS

Indocyanine Green for Injection USP contains sodium iodide and should be used with caution in patients who have a history of allergy to iodides because of the risk of anaphylaxis. (4)

5 WARNINGS AND PRECAUTIONS

- Deaths due to anaphylaxis have been reported following Indocyanine Green for Injection USP administration during cardiac catheterization. (5.1)
- Indocyanine Green for Injection USP is unstable in aqueous solution and must be used within 6 hours. (5.2)
- Radioactive iodine uptake studies should not be performed for at least a week following the use of Indocyanine Green for Injection USP. (5.3)

6 ADVERSE REACTIONS

Most common adverse reactions are anaphylactic or urticarial reactions. These have been reported in patients with and without a history of allergy to iodides. (6)

To report SUSPECTED ADVERSE REACTIONS, contact Diagnostic Green LLC at 1-844-424-3784 (1-844-ICG-DRUG) or e-mail: drugsafety@ diagnosticgreen.com; or FDA at 1-800-FDA-1088 or www.fda.gov/medwatch.

7 DRUG INTERACTIONS

Products containing sodium bisulfite reduce the absorption peak of Indocyanine Green for Injection USP in blood. (7)

FULL PRESCRIBING INFORMATION

1 INDICATIONS AND USAGE

Indocyanine Green for Injection USP is indicated:

1.1 Visual assessment of blood vessels, blood flow and related tissue perfusion

For visual assessment of blood vessels, blood flow and related tissue perfusion with OLYMPUS infrared compatible endoscopic imaging system

1.2 Visual assessment of the major extrahepatic bile duct

For visual assessment of the major extrahepatic bile ducts with OLYMPUS infrared imaging endoscopic imaging system.

1.3 Viewing intra-operative blood flow in the cerebral area

For viewing intra-operative blood flow in the cerebral area with OLYMPUS infrared compatible video microscopic imaging system

2 DOSAGE AND ADMINISTRATION

2.1 Visual assessment of blood vessels, blood flow and related tissue perfusion

Under sterile conditions, the Indocyanine Green for Injection USP powder should be dissolved with the 10 mL Sterile Water for Injection, USP provided for this product, and the solution used within 6 hours after it is prepared. If a precipitate is present, discard the solution.

The patient should be weighed and the dosage for one administration should be calculated on the basis of 0.1 mg/kg (0.04 mL/kg) - 0.3 mg/kg (0.12 mL/kg) of body weight. Multiple administrations can be performed, up to 2 mg/kg (0.8 mL/kg) per patient.

ICG should be administrated immediately before IR imaging.

Item | Note
Indocyanine Green for Injection, USP | 25 mg vials of ICG powder
Sterile Water for Injection (for dissolving ICG) | 10 mL vial of sterile water
Syringe (for injecting sterile water into the ICG vial) | Use the syringe whose minimum volume is 10 mL
Syringes (for each administration) | Considering the administration volume, select the appropriate size
Sterile normal saline (for each saline flush) | Approximately 10 – 12 mL following each ICG administration
Syringes (for each saline flush) | Use the syringe whose minimum volume is 12 mL

Prepare the syringes filled with the weight-scaled dose of ICG solution, and the syringes filled with 10 - 12 mL of normal saline for the tight bolus injection.

Immediately before IR imaging, administer the prepared dose of ICG solution intravenously. Immediately follow each ICG injection with a tight bolus injection of approximately 10 - 12 mL of normal saline.

2.2 Visual assessment of the major extrahepatic bile duct

Under sterile conditions, the Indocyanine Green for Injection USP powder should be dissolved with the 10 mL Sterile Water for Injection, USP provided for this product, and the solution used within 6 hours after it is prepared. If a precipitate is present, discard the solution.

The dosage for one administration should be 3.0 mg (1.2 mL) per patient. Multiple administration can be performed, up to 2 mg/kg (0.8 mL/kg) per patient.

ICG should be administrated at least 30 minutes prior to IR imaging.

Item | Note
Indocyanine Green for Injection, USP | 25 mg vials of ICG powder
Sterile Water for Injection (for dissolving ICG) | 10 mL vial of sterile water
Syringe (for injecting sterile water into the ICG vial) | Use the syringe whose minimum volume is 10 mL
Syringes (for each administration) | Considering the administration volume, select the appropriate size
Sterile normal saline (for each saline flush) | Approximately 10 – 12 mL following each ICG administration
Syringes (for each saline flush) | Use the syringe whose minimum volume is 12 mL

Prepare the syringes filled with 3.0 mg (1.2 mL) of ICG solution, and the syringes filled with 10 - 12 mL of normal saline for the tight bolus.

At least 30 minutes prior to IR imaging, administer the prepared dose of ICG solution intravenously. Immediately follow each ICG injection with a tight bolus injection of approximately 10 - 12 mL of normal saline.

2.3 Viewing intra-operative blood flow in the cerebral area

Under sterile conditions, the Indocyanine Green for Injection USP powder should be dissolved with the 10 mL Sterile Water for Injection, USP provided for this product, and the solution used within 6 hours after it is prepared. If a precipitate is present, discard the solution.

The patient should be weighed and the dosage for one administration should be calculated on the basis of 0.1 mg/kg (0.04 mL/kg) - 0.3 mg/kg (0.12 mL/kg) of body weight. Multiple administration can be performed, up to 2 mg/kg (0.8 mL/kg) per patient.

ICG should be administrated immediately before IR imaging.

Item | Note
Indocyanine Green for Injection, USP | 25 mg vials of ICG powder
Sterile Water for Injection (for dissolving ICG) | 10 mL vial of sterile water
Syringe (for injecting sterile water into the ICG vial) | Use the syringe whose minimum volume is 10 mL
Syringes (for each administration) | Considering the administration volume, select the appropriate size
Sterile normal saline (for each saline flush) | Approximately 10 – 12 mL following each ICG administration
Syringes (for each saline flush) | Use the syringe whose minimum volume is 12 mL

Prepare the syringes filled with the weight-scaled dose of ICG solution, and the syringes filled with 10 - 12 mL of normal saline for the tight bolus.

Immediately before IR imaging, administer the prepared dose of ICG solution intravenously. Immediately follow each ICG injection with a tight bolus injection of approximately 10 - 12 mL of normal saline.

3 DOSAGE FORMS AND STRENGTHS

Indocyanine Green for Injection USP is a sterile, lyophilized green powder containing 25 mg of indocyanine green with no more than 5% sodium iodide.

4 CONTRAINDICATIONS

Indocyanine Green for Injection USP contains sodium iodide and should be used with caution in patients who have a history of allergy to iodides because of the risk of anaphylaxis.

5 WARNINGS AND PRECAUTIONS

5.1 Anaphylaxis

Deaths from anaphylaxis have been reported following Indocyanine Green for Injection USP administration during cardiac catheterization.

5.2 Drug Instability

Indocyanine Green for Injection USP is unstable in aqueous solution and must be used within 6 hours. However, the dye is stable in plasma and whole blood so that samples obtained in discontinuous sampling techniques may be read hours later. Sterile techniques should be used in handling the dye solution as well as in the performance of the dilution curves. If a precipitate is present, discard the solution.

5.3 Drug/Laboratory Test Interactions

Radioactive iodine uptake studies should not be performed for at least a week following the use of Indocyanine Green for Injection USP.

6 ADVERSE REACTIONS

Anaphylactic or urticarial reactions have been reported in patients with or without history of allergy to iodides. If such reactions occur, treat with the appropriate agents, e.g., epinephrine, antihistamines, and corticosteroids.

7 DRUG INTERACTIONS

Preparations containing sodium bisulfite including some heparin products reduce the absorption peak of Indocyanine Green for Injection USP in blood and, therefore, should not be used as an anticoagulant for the collection of samples for analysis.

8 USE IN SPECIFIC POPULATIONS

8.1 Pregnancy

Animal reproduction studies have not been conducted with Indocyanine Green for Injection USP. It is also not known whether Indocyanine Green for Injection USP can cause fetal harm when administered to a pregnant woman or can affect reproduction capacity. Indocyanine Green for Injection USP should be given to a pregnant woman only if clearly indicated.

8.3 Nursing Mothers

It is not known whether this drug is excreted in human milk. Because many drugs are excreted in human milk, caution should be exercised when Indocyanine Green for Injection USP is administered to a nursing woman.

8.4 Pediatric Use

The safety and effectiveness of indocyanine green for visual assessment of blood vessels, blood flow and related tissue perfusion, for visual assessment of the major extrahepatic bile duct and for intra-operative blood flow in the cerebral area using this IR imaging application has not been evaluated in pediatric patients.

8.5 Geriatric Use

No overall differences in safety or effectiveness have been observed between elderly and adult patients.

10 OVERDOSAGE

There are no data available describing the signs, symptoms, or laboratory findings accompanying overdosage. The LD50 after intravenous administration ranges between 60 and 80 mg/kg in mice, 50 and 70 mg/kg in rats and 50 and 80 mg/kg in rabbits. Based on body surface area, these doses are 2.4 to 13-fold the maximum recommended human (MRHD) dose of 2 mg/kg for indicator-dilution studies, 10 to 52-fold the MRHD of 0.5 mg/kg for hepatic-function studies, and 7 to 39-fold the MRHD of 0.67 mg/kg for ophthalmic angiography studies.

11 DESCRIPTION

Indocyanine Green for Injection USP is a sterile, lyophilized green powder containing 25 mg of indocyanine green with no more than 5% sodium iodide. It is packaged with Sterile Water for Injection, USP used to dissolve the indocyanine green. Indocyanine Green for Injection USP is to be administered intravenously.

Indocyanine green is a water soluble, tricarbocyanine dye with a peak spectral absorption at 800 nm. The chemical name for Indocyanine Green is 1 H-Benz[e]indolium, 2-[7-[1,3-dihydro-1,1-dimethyl-3-(4-sulfobutyl)-2H-benz[e] indol-2-ylidene]-1,3,5-heptatrienyl]-1,1-dimethyl-3-(4-sulfobutyl)-,hydroxide, inner salt, sodium salt. Indocyanine Green for Injection USP has a pH of approximately 6.5 when reconstituted. Each vial of Indocyanine Green for Injection USP contains 25 mg of indocyanine green as a sterile lyophilized powder.

12 CLINICAL PHARMACOLOGY

Indocyanine Green for Injection USP permits recording of the indicator-dilution curves for both diagnostic and research purposes independently of fluctuations in oxygen saturation. Following intravenous injection, Indocyanine Green for Injection USP is rapidly bound to plasma protein, of which albumin is the principle carrier (95%). Indocyanine Green for Injection USP undergoes no significant extrahepatic or enterohepatic circulation; simultaneous arterial and venous blood estimations have shown negligible renal, peripheral, lung or cerebro-spinal uptake of the dye. Indocyanine Green for Injection USP is taken up from the plasma almost exclusively by the hepatic parenchymal cells and is secreted entirely into the bile. After biliary obstruction, the dye appears in the hepatic lymph, independently of the bile, suggesting that the biliary mucosa is sufficiently intact to prevent diffusion of the dye, though allowing diffusion of bilirubin. These characteristics make Indocyanine Green for Injection USP a helpful index of hepatic function.

The peak absorption and emission of Indocyanine Green for Injection USP lie in a region (800 to 850 nm) where transmission of energy by the pigment epithelium is more efficient than in the region of visible light energy. Indocyanine Green for Injection USP also has the property of being nearly 98% bound to blood protein, and therefore, excessive dye extravasation does not take place in the highly fenestrated choroidal vasculature. It is, therefore, useful in both absorption and fluorescence infrared angiography of the choroidal vasculature when using appropriate filters and film in a fundus camera.

The plasma fractional disappearance rate at the recommended 0.5 mg/kg dose has been reported to be significantly greater in women than in men, although there was no significant difference in the calculated value for clearance.

13 NONCLINICAL TOXICOLOGY

13.1 Carcinogenesis, Mutagenesis, Impairment of Fertility

No studies have been performed to evaluate the carcinogenicity, mutagenicity, or impairment of fertility.

16 HOW SUPPLIED/STORAGE AND HANDLING

Indocyanine Green for Injection USP is supplied in a kit (NDC 73624-424-02) containing six 25 mg Indocyanine Green for Injection USP vials and six 10 mL Sterile Water for Injection, USP plastic vials:

NDC 70100-424-01 Indocyanine Green for Injection USP vial. 25 mg fill in 25 mL vial.

NDC 63323-185-10 (or NDC 0409-4887-17) Sterile Water for Injection, USP, 10 mL fill in 10 mL plastic vials.

STORAGE: Store at 20° to 25°C (68° to 77°F).
[See USP Controlled Room Temperature].

Manufactured by:
Patheon Italia S.p.A.
20900 Monza (MB), ITALY

Distributed by:
OLYMPUS AMERICA INC.
3500 Corporate Parkway
P.O. Box 610
Center Valley, PA, 18034-0610

Sterile Water for Injection,
USP is manufactured by:
Fresenius Kabi USA, LLC
Grand Island, NY 14072 USA
or
Hospira, Inc.
Rocky Mount, NC 27804 USA

50652
06/2020

PRINCIPAL DISPLAY PANEL - Carton Label

Carton Label

NDC 73624-424-02

Indocyanine Green
for Injection, USP

For Intravenous Administration 25 mg/Vial Kit Rx Only - Sterile

Distributed by:
OLYMPUS AMERICA INC.

Back Panel

NDC 73624-424-02

DIRECTIONS FOR USE ENCLOSED
CAUTION: To ensure accurate readings,
Indocyanine Green, USP dissolved in Sterile Water
for Injection, USP must be used within 6 hours.
STORAGE: Store at 20° to 25°C (68° to 77°F)
[See USP Controlled Room Temperature].

USAGE: See package insert for dosage information.
Contents: Six Indocyanine Green for Injection, USP
vials (25 mg each)
Six Sterile Water for Injection, USP Vials
(10 mL each)

Indocyanine Green
for Injection, USP

For Intravenous Administration 25 mg/Vial Kit Rx Only - Sterile

Right Panel

Indocyanine Green
for Injection, USP

Distributed by:
OLYMPUS AMERICA INC.
3500 Corporate Parkway, P.O. Box 610,
Center Valley, PA 1834-0610, U.S.A.

Manufactured by:
Patheon Italia S.p.A.
20900 Monza (Milano) ITALY

Sterile Water Manufactured by:
Hospira, Inc.
Rocky Mount, NC 27804
or
Fresenius Kabi USA, LLC
Grand Island, NY 14072

4/2020

PRINCIPAL DISPLAY PANEL - Vial Label

Vial Label

NDC 70100-424-01

Indocyanine Green
for Injection, USP

25 mg/Vial

Single-Patient-Use
After reconstitution, use within 6 hours.

Rx only Sterile

Distributed by: Diagnostic Green LLC

50428
04/2022

Lot No.
Exp.:

PRINCIPAL DISPLAY PANEL - STERILE WATER VIAL

Sterile Water Label

10 mL Single-dose

Sterile Water
for Injection, USP

FOR DRUG DILUENT USE

LOT ##-###-AA
EXP DMMMYYYY

Rx only NDC 0409-4887-17

Contains no antimicrobial or other added
substance. Sterile, nonpyrogenic. Do not give
intravenously unless rendered nearly isotonic.

Distributed by RL-7603
Hospira, Inc., Lake Forest, IL 60045 USA